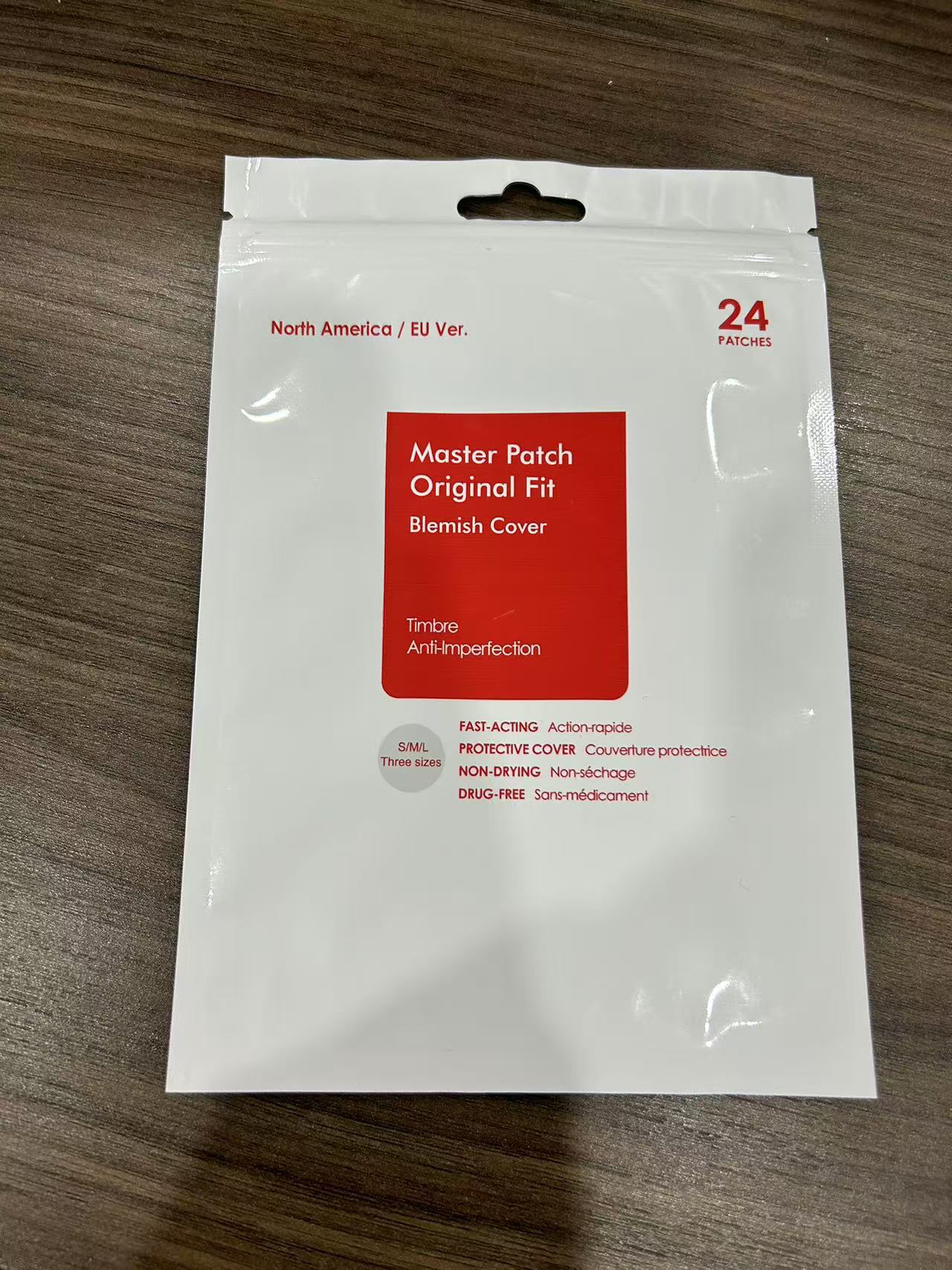 DRUG LABEL: Acne Patch
NDC: 84766-0003 | Form: PATCH
Manufacturer: COMFMET LIMITED
Category: otc | Type: HUMAN OTC DRUG LABEL
Date: 20241022

ACTIVE INGREDIENTS: GELATIN 20 g/100 g
INACTIVE INGREDIENTS: DIOCTYL ADIPATE; POLYETHYLENE TEREPHTHALATE (INTRINSIC VISCOSITY 0.40-0.70); CARBOXYMETHYLCELLULOSE SODIUM (0.7 CARBOXYMETHYL SUBSTITUTION PER SACCHARIDE; 100-200 MPA.S AT 1%); POLYVINYL ALCOHOL; POLYURETHANE-34 (40 MPA, TENSILE STRENGTH OF FILM AT BREAK)

Active Ingredients

Gelatin 20%

PurPose

Acne treatment

Uses

treats and helps prevent acne

Warnings

For external use only

When using this product

keep away from eyes, lips and mouth. lf contact occurs, flush thoroughly with water.

skin irritation and dryness is more likely to occur if you use another topical acne medication at the same time If irritation occurs, only use one topical acne medication at a time.

Keep Out Of Reach of children

lf pregnant or breast-feeding,ask a healthcare professional before use. lf accidental ingestion and adverse reaction occurs, get medical help or contact a Poison Control Center.

DESCRIPTION

cleanse skin thoroughly before applying this product
apply patch(es) to affected area(s)
to remove, gently peel back patch and discard
because excessive drying of the skin may occur, start with 1 application daily, then gradually increase to 2 or 3 times daily if needed or as directed by a doctor
if bothersome dryness or peeling occurs, reduce application to once a day or every other day

Other information

store in a cool dry place, away from direct sunlight.

INACTIVE INGREDIENT

Sodium carboxy methyl cellulose,
Dioctyl adipate,
Hot melt adhesive,
Polyurethane film,
Polyethylene terephthalate,

QUESTIONS

Email: commet515@gmail.com

DOSAGE AND ADMINISTRATION

After washing face, apply directly to the pimple, once in the morning and once in the evening